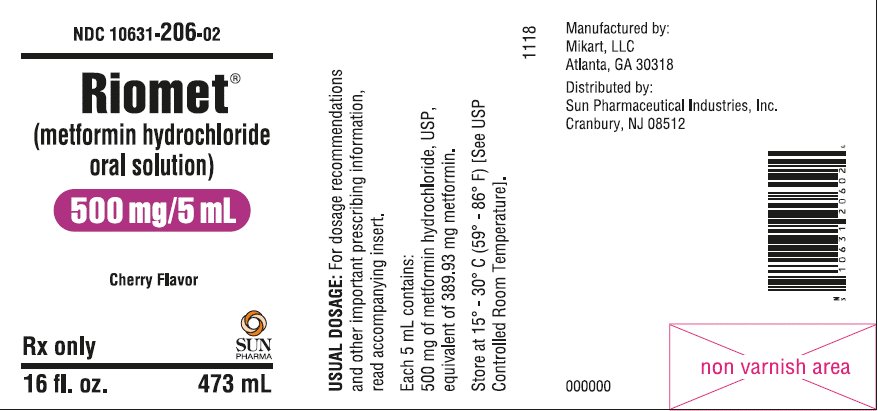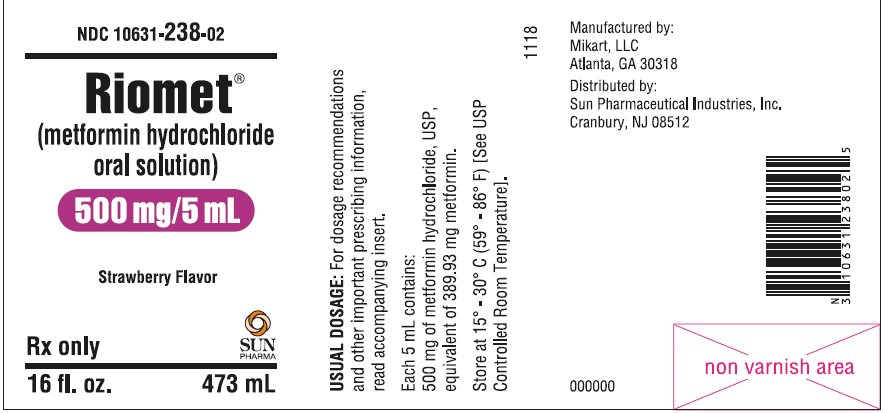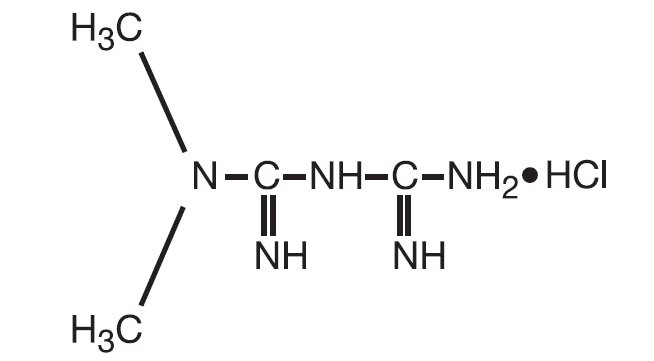 DRUG LABEL: Riomet
NDC: 10631-238 | Form: SOLUTION
Manufacturer: Sun Pharmaceutical Industries, Inc.
Category: prescription | Type: HUMAN PRESCRIPTION DRUG LABEL
Date: 20181206

ACTIVE INGREDIENTS: METFORMIN HYDROCHLORIDE 500 mg/5 mL
INACTIVE INGREDIENTS: HYDROCHLORIC ACID; POTASSIUM BICARBONATE; XYLITOL; SUCRALOSE; PROPYLENE GLYCOL; GLYCERIN

HIGHLIGHTS OF PRESCRIBING INFORMATION

These highlights do not include all the information needed to use RIOMET safely and effectively. See full prescribing information for RIOMET.
RIOMET® (metformin hydrochloride) solution, for oral use
Initial U.S. Approval: 1995

WARNING: LACTIC ACIDOSIS

See full prescribing information for complete boxed warning

- Postmarketing cases of metformin-associated lactic acidosis have resulted in death, hypothermia, hypotension, and resistant bradyarrhythmias. Symptoms included malaise, myalgias, respiratory distress, somnolence, and abdominal pain. Laboratory abnormalities included elevated blood lactate levels, anion gap acidosis, increased lactate/pyruvate ratio; and metformin plasma levels generally > 5 mcg/mL. (5.1)
- Risk factors include renal impairment, concomitant use of certain drugs, age ≥ 65 years old, radiological studies with contrast, surgery and other procedures, hypoxic states, excessive alcohol intake, and hepatic impairment. Steps to reduce the risk of and manage metformin-associated lactic acidosis in these high risk groups are provided in the Full Prescribing Information. (5.1)
- If lactic acidosis is suspected, discontinue RIOMET and institute general supportive measures in a hospital setting. Prompt hemodialysis is recommended. (5.1)

1 INDICATIONS AND USAGE

RIOMET is a biguanide indicated as an adjunct to diet and exercise to improve glycemic control in adults and pediatric patients 10 years of age and older with type 2 diabetes mellitus. (1)

2 DOSAGE AND ADMINISTRATION

Adult Dosage for RIOMET:

- Starting dose: 500 mg (5 mL) orally twice a day or 850 mg (8.5 mL) once a day, with meals (2.1)
- Increase the dose in increments of 500 mg (5 mL) weekly or 850 mg (8.5 mL) every 2 weeks, up to a maximum dose of 2,550 mg (25.5 mL) per day, given in divided doses
  (2.1)
- Doses above 2,000 mg (20 mL) may be better tolerated given in divided doses 3 times a day with meals (2.1)

Pediatric Dosage for RIOMET:

- Starting dose: 500 mg (5 mL) orally twice a day, with meals (2.2)
- Increase dosage in increments of 500 mg (5 mL) weekly up to a maximum of
  2,000 mg (20 mL) per day, given in divided doses twice daily (2.2)

Renal Impairment:

- Prior to initiation, assess renal function with estimated glomerular
  filtration rate (eGFR) (2.3)
- Do not use in patients with eGFR below 30 mL/minute/1.73 m^2 (2.3)
- Initiation is not recommended in patients with eGFR between 30 to 45 mL/minute/1.73 m^2 (2.3)
- Assess risk/benefit of continuing RIOMET if eGFR falls below 45 mL/minute/1.73 m^2 (2.3)
- Discontinue if eGFR falls below 30 mL/minute/1.73 m^2 (2.3)

Discontinuation for Iodinated Contrast Imaging Procedures:

- RIOMET may need to be discontinued at time of, or prior to, iodinated contrast imaging procedures (2.4)

3 DOSAGE FORMS AND STRENGTHS

Oral Solution: 500 mg per 5 mL (100 mg/mL) in cherry and strawberry flavor (3)

4 CONTRAINDICATIONS

- Severe renal impairment (eGFR below 30 mL/min/1.73 m^2) (4, 5.1)
- Hypersensitivity to metformin (4)
- Acute or chronic metabolic acidosis, including diabetic ketoacidosis, with or without coma. (4)

5 WARNINGS AND PRECAUTIONS

- Lactic acidosis: See boxed warning. (5.1)
- Vitamin B12 deficiency: Metformin may lower vitamin B12 levels. Measure hematological parameters annually and vitamin B12 at 2 to 3 year intervals and manage any abnormalities. (5.2)
- Hypoglycemia with Concomitant Use with Insulin and Insulin Secretagogues: Increased risk of hypoglycemia when used in combination with insulin and/or an insulin secretagogue. Lower dose of insulin or insulin secretagogue may be required (5.3)

6 ADVERSE REACTIONS

The most common adverse reactions are diarrhea, nausea/vomiting, flatulence, asthenia, indigestion, abdominal discomfort, and headache. (6.1)

To report SUSPECTED ADVERSE REACTIONS, contact Sun Pharmaceutical Industries, Inc. at 1-800-818-4555 or FDA at 1-800-FDA-1088 or http://www.fda.gov/medwatch

7 DRUG INTERACTIONS

- Carbonic anhydrase inhibitors may increase risk of lactic acidosis. Consider more frequent monitoring (7)
- Drugs that reduce metformin clearance (such as ranolazine, vandetanib, dolutegravir, and cimetidine) may increase the accumulation of metformin. Consider the benefits and risks of concomitant use (7)
- Alcohol can potentiate the effect of metformin on lactate metabolism. Warn patients against excessive alcohol intake (7)

8 USE IN SPECIFIC POPULATIONS

- Females and Males of Reproductive Potential: Advise premenopausal females of the potential for an unintended pregnancy. (8.3)
- Geriatric Use: Assess renal function more frequently. (8.5)
- Hepatic Impairment: Avoid use in patients with hepatic impairment. (8.7)

FULL PRESCRIBING INFORMATION

WARNING: LACTIC ACIDOSIS

Postmarketing cases of metformin-associated lactic acidosis have resulted in death, hypothermia, hypotension, and resistant bradyarrhythmias. The onset of metformin‑ associated lactic acidosis is often subtle, accompanied only by nonspecific symptoms such as malaise, myalgias, respiratory distress, somnolence, and abdominal pain. Metformin‑ associated lactic acidosis was characterized by elevated blood lactate levels (>5 mmol/Liter), anion gap acidosis (without evidence of ketonuria or ketonemia), an increased lactate/pyruvate ratio; and metformin plasma levels generally >5 mcg/mL [see Warnings and Precautions (5.1)].

Risk factors for metformin-associated lactic acidosis include renal impairment, concomitant use of certain drugs (e.g. carbonic anhydrase inhibitors such as topiramate), age 65 years old or greater, having a radiological study with contrast, surgery and other procedures, hypoxic states (e.g., acute congestive heart failure), excessive alcohol intake, and hepatic impairment.

Steps to reduce the risk of and manage metformin-associated lactic acidosis in these high risk groups are provided [see Dosage and Administration (2.3), Contraindications (4), Warnings and Precautions (5.1)].

If metformin-associated lactic acidosis is suspected, immediately discontinue RIOMET and institute general supportive measures in a hospital setting. Prompt hemodialysis is recommended [see Warnings and Precautions (5.1)].

1 INDICATIONS AND USAGE

RIOMET is indicated as an adjunct to diet and exercise to improve glycemic control in adults and pediatric patients 10 years of age and older with type 2 diabetes mellitus.

2 DOSAGE AND ADMINISTRATION

2.1 Adult Dosage

- Measure the RIOMET dose in the RIOMET specific dosing cup.
- The recommended starting dose of RIOMET is 500 mg (5 mL) orally twice a day or 850 mg (8.5 mL) once a day, given with meals.
- Increase the dose in increments of 500 mg (5 mL) weekly or 850 mg (8.5 mL) every 2 weeks on the basis of glycemic control and tolerability, up to a maximum dose of 2,550 mg (25.5 mL) per day, given in divided doses.
- Doses above 2,000 mg (20 mL) may be better tolerated given in divided doses 3 times a day with meals.

2.2 Pediatric Dosage

- Measure the RIOMET dose in the RIOMET specific dosing cup.
- The recommended starting dose of RIOMET for pediatric patients 10 years of age and older is 500 mg (5 mL) orally twice a day, given with meals.
- Increase dosage in increments of 500 mg (5 mL) weekly on the basis of glycemic control and tolerability, up to a maximum of 2,000 mg (20 mL) per day, given in divided doses twice daily.

2.3 Recommendations for Use in Renal Impairment

- Assess renal function prior to initiation of RIOMET and periodically thereafter.
- RIOMET is contraindicated in patients with an estimated glomerular filtration rate (eGFR) below 30 mL/minute/1.73 m^2.
- Initiation of RIOMET in patients with an eGFR between 30 to 45 mL/minute/1.73 m^2 is not recommended.
- In patients taking RIOMET whose eGFR later falls below 45 mL/min/1.73 m^2, assess the benefit risk of continuing therapy.
- Discontinue RIOMET if the patient’s eGFR later falls below 30 mL/minute/1.73 m^2 [see Warnings and Precautions (5.1)].

2.4 Discontinuation for Iodinated Contrast Imaging Procedures

- Discontinue RIOMET at the time of, or prior to, an iodinated contrast imaging procedure in patients with an eGFR between 30 and 60 mL/min/1.73 m^2; in patients with a history of liver disease, alcoholism, or heart failure; or in patients who will be administered intra-arterial iodinated contrast. Re-evaluate eGFR 48 hours after the imaging procedure; restart RIOMET if renal function is stable.

3 DOSAGE FORMS AND STRENGTHS

Oral solution: 500 mg per 5 mL (100 mg/mL) clear solution in cherry and strawberry flavor

4 CONTRAINDICATIONS

1. RIOMET is contraindicated in patients with:
2. Severe renal impairment (eGFR below 30 mL/min/1.73 m^2) [see Warnings and Precautions (5.1)].
3. Hypersensitivity to metformin.
4. Acute or chronic metabolic acidosis, including diabetic ketoacidosis, with or without coma.

5 WARNINGS AND PRECAUTIONS

5.1 Lactic Acidosis

- There have been postmarketing cases of metformin-associated lactic acidosis, including fatal cases. These cases had a subtle onset and were accompanied by nonspecific symptoms such as malaise, myalgias, abdominal pain, respiratory distress, or increased somnolence; however, hypotension and resistant bradyarrhythmias have occurred with severe acidosis. Metformin‑associated lactic acidosis was characterized by elevated blood lactate concentrations (> 5 mmol/L), anion gap acidosis (without evidence of ketonuria or ketonemia), and an increased lactate: pyruvate ratio; metformin plasma levels were generally > 5 mcg/mL. Metformin decreases liver uptake of lactate increasing lactate blood levels which may increase the risk of lactic acidosis, especially in patients at risk.
- If metformin-associated lactic acidosis is suspected, general supportive measures should be instituted promptly in a hospital setting, along with immediate discontinuation of RIOMET. In RIOMET treated patients with a diagnosis or strong suspicion of lactic acidosis, prompt hemodialysis is recommended to correct the acidosis and remove accumulated metformin (metformin hydrochloride is dialyzable with a clearance of up to 170 mL/min under good hemodynamic conditions). Hemodialysis has often resulted in reversal of symptoms and recovery.
- Educate patients and their families about the symptoms of lactic acidosis and, if these symptoms occur, instruct them to discontinue RIOMET and report these symptoms to their healthcare provider.
- For each of the known and possible risk factors for metformin-associated lactic acidosis, recommendations to reduce the risk of and manage metformin-associated lactic acidosis are provided below:
- Before initiating RIOMET, obtain an estimated glomerular filtration rate (eGFR).
- RIOMET is contraindicated in patients with an eGFR less than 30 mL/min/1.73 m^2 [see Contraindications (4)].
- Initiation of RIOMET is not recommended in patients with eGFR between 30 to 45 mL/min/1.73 m^2.
- Obtain an eGFR at least annually in all patients taking RIOMET. In patients at risk for the development of renal impairment (e.g., the elderly), renal function should be assessed more frequently.
- In patients taking RIOMET whose eGFR falls below 45 mL/min/1.73 m^2, assess the benefit and risk of continuing therapy.
- Renal impairment—The postmarketing metformin-associated lactic acidosis cases primarily occurred in patients with significant renal impairment.
- The risk of metformin accumulation and metformin-associated lactic acidosis increases with the severity of renal impairment because metformin is substantially excreted by the kidney. Clinical recommendations based upon the patient’s renal function include [see Dosage and Administration (2.3), Clinical Pharmacology (12.3)]:
- Before initiating RIOMET, obtain an estimated glomerular filtration rate (eGFR).
- RIOMET is contraindicated in patients with an eGFR less than 30 mL/min/1.73 m^2 [see Contraindications (4)].
- Initiation of RIOMET is not recommended in patients with eGFR between 30 to 45 mL/min/1.73 m^2.
- Obtain an eGFR at least annually in all patients taking RIOMET. In patients at risk for the development of renal impairment (e.g., the elderly), renal function should be assessed more frequently.
- In patients taking RIOMET whose eGFR falls below 45 mL/min/1.73 m^2, assess the benefit and risk of continuing therapy.
- Drug interactions — The concomitant use of RIOMET with specific drugs may increase the risk of metformin-associated lactic acidosis: those that impair renal function, result in significant hemodynamic change, interfere with acid-base balance, or increase metformin accumulation. Consider more frequent monitoring of patients [see Drug Interactions (7)].
- Age 65 or greater — The risk of metformin-associated lactic acidosis increases with the patient’s age because elderly patients have a greater likelihood of having hepatic, renal, or cardiac impairment than younger patients. Assess renal function more frequently in elderly patients.
- Radiologic studies with contrast — Administration of intravascular iodinated contrast agents in metformin-treated patients has led to an acute decrease in renal function and the occurrence of lactic acidosis. Stop RIOMET at the time of, or prior to, an iodinated contrast imaging procedure in patients with an eGFR between 30 and 60 mL/min/1.73 m^2; in patients with a history of hepatic impairment, alcoholism or heart failure; or in patients who will be administered intra-arterial iodinated contrast. Re-evaluate eGFR 48 hours after the imaging procedure, and restart RIOMET if renal function is stable.
- Surgery and other procedures — Withholding of food and fluids during surgical or other procedures may increase the risk for volume depletion, hypotension, and renal impairment. RIOMET should be temporarily discontinued while patients have restricted food and fluid intake.
- Hypoxic states — Several of the postmarketing cases of metformin-associated lactic acidosis occurred in the setting of acute congestive heart failure (particularly when accompanied by hypoperfusion and hypoxemia). Cardiovascular collapse (shock), acute myocardial infarction, sepsis, and other conditions associated with hypoxemia have been associated with lactic acidosis and may cause prerenal azotemia. When such an event occurs, discontinue RIOMET.
- Excessive alcohol intake — Alcohol potentiates the effect of metformin on lactate metabolism. Patients should be warned against excessive alcohol intake while receiving RIOMET.
- Hepatic impairment — Patients with hepatic impairment have developed cases of metformin-associated lactic acidosis. This may be due to impaired lactate clearance resulting in higher lactate blood levels. Therefore, avoid use of RIOMET in patients with clinical or laboratory evidence of hepatic disease.

5.2 Vitamin B12 Deficiency

1. In clinical trials of 29-week duration with metformin hydrochloride (HCl) tablets, a decrease to subnormal levels of previously normal serum vitamin B12 levels was observed in approximately 7% of patients. Such decrease, possibly due to interference with B12 absorption from the B12-intrinsic factor complex, may be associated with anemia but appears to be rapidly reversible with discontinuation of metformin or vitamin B12 supplementation. Certain individuals (those with inadequate vitamin B12 or calcium intake or absorption) appear to be predisposed to developing subnormal vitamin B12 levels. Measure hematologic parameters on an annual basis and vitamin B12 at 2 to 3 year intervals in patients on RIOMET and manage any abnormalities [see Adverse Reactions (6.1)].

5.3 Hypoglycemia with Concomitant Use with Insulin and Insulin Secretagogues

Insulin and insulin secretagogues (e.g., sulfonylurea) are known to cause hypoglycemia. RIOMET may increase the risk of hypoglycemia when combined with insulin and/or an insulin secretagogue. Therefore, a lower dose of insulin or insulin secretagogue may be required to minimize the risk of hypoglycemia when used in combination with RIOMET [see Drug Interactions (7)].

5.4 Macrovascular Outcomes

There have been no clinical studies establishing conclusive evidence of macrovascular risk reduction with RIOMET.

6 ADVERSE REACTIONS

- The following adverse reactions are also discussed elsewhere in the labeling:
- Lactic Acidosis [see Boxed Warning and Warnings and Precautions (5.1)]
- Vitamin B12 Deficiency [see Warnings and Precautions (5.2)]
- Hypoglycemia [see Warnings and Precautions (5.3)]

6.1 Clinical Studies Experience

1. Because clinical trials are conducted under widely varying conditions, adverse reaction rates observed in the clinical trials of a drug cannot be directly compared to rates in the clinical trials of another drug and may not reflect the rates observed in practice.
2. In a U.S. clinical trial of metformin HCl tablets in patients with type 2 diabetes mellitus, a total of 141 patients received metformin HCl tablets up to 2,550 mg per day. Adverse reactions reported in greater than 5% of patients treated with metformin HCl tablets and that were more common than in placebo-treated patients, are listed in Table 1.
3. Table 1: Adverse Reactions from a Clinical Trial of Metformin HCl Tablets Occurring >5% and More Common than Placebo in Patients with Type 2 Diabetes Mellitus

 | 1. Metformin HCl Tablets (n = 141) | 1. Placebo; (n = 145)
1. Diarrhea | 1. 53% | 1. 12%
1. Nausea/Vomiting | 1. 26% | 1. 8%
1. Flatulence | 1. 12% | 1. 6%
1. Asthenia | 1. 9% | 1. 6%
1. Indigestion | 1. 7% | 1. 4%
1. Abdominal Discomfort | 1. 6% | 1. 5%
1. Headache | 1. 6% | 1. 5%

1. Diarrhea led to discontinuation of metformin HCl tablets in 6% of patients. Additionally, the following adverse reactions were reported in ≥ 1% to ≤ 5% of patients treated with metformin HCl tablets and were more commonly reported than placebo: abnormal stools, hypoglycemia, myalgia, lightheaded, dyspnea, nail disorder, rash, sweating increased, taste disorder, chest discomfort, chills, flu syndrome, flushing, palpitation.
2. Pediatric Patients
3. In clinical trials with metformin HCl tablets in pediatric patients with type 2 diabetes mellitus, the profile of adverse reactions was similar to that observed in adults.
4. Laboratory Tests
5. Vitamin B12 Concentrations
6. In clinical trials of 29-week duration with metformin HCl tablets, a decrease to subnormal levels of previously normal serum vitamin B12 levels was observed in approximately 7% of patients.

6.2 Postmarketing Experience

- The following adverse reactions have been identified during post approval use of metformin. Because these reactions are reported voluntarily from a population of uncertain size, it is not always possible to reliably estimate their frequency or establish a causal relationship to drug exposure.
- Cholestatic, hepatocellular, and mixed hepatocellular liver injury have been reported with postmarketing use of metformin.

7 DRUG INTERACTIONS

1. Table 2 presents clinically significant drug interactions with RIOMET.
2. Table 2: Clinically Significant Drug Interactions with RIOMET

1. Carbonic Anhydrase Inhibitors
1. Clinical Impact: | 1. Carbonic anhydrase inhibitors frequently cause a decrease in serum bicarbonate and induce non-anion gap, hyperchloremic metabolic acidosis. Concomitant use of these drugs with RIOMET may increase the risk for lactic acidosis.
1. Intervention: | 1. Consider more frequent monitoring of these patients.
1. Examples: | 1. Topiramate, zonisamide, acetazolamide or dichlorphenamide.
1. Drugs that Reduce RIOMET Clearance
1. Clinical Impact: | 1. Concomitant use of drugs that interfere with common renal tubular transport systems involved in the renal elimination of metformin (e.g., organic cationic transporter-2 [OCT2] / multidrug and toxin extrusion [MATE] inhibitors) could increase systemic exposure to metformin and may increase the risk for lactic acidosis [see Clinical Pharmacology (12.3)].
1. Intervention: | 1. Consider the benefits and risks of concomitant use with RIOMET.
1. Examples: | 1. Ranolazine, vandetanib, dolutegravir, and cimetidine.
1. Alcohol
1. Clinical Impact: | 1. Alcohol is known to potentiate the effect of metformin on lactate metabolism.
1. Intervention: | 1. Warn patients against excessive alcohol intake while receiving RIOMET.
1. Insulin Secretagogues or Insulin
1. Clinical Impact: | 1. Coadministration of RIOMET with an insulin secretagogue (e.g., sulfonylurea) or insulin may increase the risk of hypoglycemia.
1. Intervention: | 1. Patients receiving an insulin secretagogue or insulin may require lower doses of the insulin secretagogue or insulin.
1. Drugs Affecting Glycemic Control
1. Clinical Impact: | 1. Certain drugs tend to produce hyperglycemia and may lead to loss of glycemic control.
1. Intervention: | 1. When such drugs are administered to a patient receiving RIOMET, observe the patient closely for loss of blood glucose control. When such drugs are withdrawn from a patient receiving RIOMET, observe the patient closely for hypoglycemia.
1. Examples: | 1. Thiazides and other diuretics, corticosteroids, phenothiazines, thyroid products, estrogens, oral contraceptives, phenytoin, nicotinic acid, sympathomimetics, calcium channel blockers, and isoniazid.

8 USE IN SPECIFIC POPULATIONS

8.1 Pregnancy

1. Risk Summary
2. Limited data with RIOMET in pregnant women are not sufficient to determine a drug-associated risk for major birth defects or miscarriage. Published studies with metformin use during pregnancy have not reported a clear association with metformin and major birth defect or miscarriage risk [see Data]. There are risks to the mother and fetus associated with poorly controlled diabetes mellitus in pregnancy [see Clinical Considerations].
3. No adverse developmental effects were observed when metformin was administered to pregnant Sprague Dawley rats and rabbits during the period of organogenesis at doses up to 2- and 5‑ times, respectively, a 2,550 mg clinical dose, based on body surface area [see Data].
4. The estimated background risk of major birth defects is 6 to 10% in women with pre-gestational diabetes mellitus with an HbA1C >7 and has been reported to be as high as 20 to 25% in women with a HbA1C >10. The estimated background risk of miscarriage for the indicated population is unknown. In the U.S. general population, the estimated background risk of major birth defects and miscarriage in clinically recognized pregnancies is 2 to 4% and 15 to 20%, respectively.
5. Clinical Considerations
6. Disease-associated maternal and/or embryo/fetal risk
7. Poorly-controlled diabetes mellitus in pregnancy increases the maternal risk for diabetic ketoacidosis, pre-eclampsia, spontaneous abortions, preterm delivery, stillbirth and delivery complications. Poorly controlled diabetes mellitus increases the fetal risk for major birth defects, stillbirth, and macrosomia related morbidity.
8. Data
9. Human Data
10. Published data from post-marketing studies have not reported a clear association with metformin and major birth defects, miscarriage, or adverse maternal or fetal outcomes when metformin was used during pregnancy. However, these studies cannot definitely establish the absence of any metformin-associated risk because of methodological limitations, including small sample size and inconsistent comparator groups.
11. Animal Data
12. Metformin hydrochloride did not adversely affect development outcomes when administered to pregnant rats and rabbits at doses up to 600 mg/kg/day. This represents an exposure of about 2 and 5 times a 2,550 mg clinical dose based on body surface area comparisons for rats and rabbits, respectively. Determination of fetal concentrations demonstrated a partial placental barrier to metformin.

8.2 Lactation

- Risk Summary
- Limited published studies report that metformin is present in human milk [see Data]. However, there is insufficient information to determine the effects of metformin on the breastfed infant and no available information on the effects of metformin on milk production. Therefore, the developmental and health benefits of breastfeeding should be considered along with the mother’s clinical need for RIOMET and any potential adverse effects on the breastfed child from RIOMET or from the underlying maternal condition.
- Data
- Published clinical lactation studies report that metformin is present in human milk which resulted in infant doses approximately 0.11% to 1% of the maternal weight-adjusted dosage and a milk/plasma ratio ranging between 0.13 and 1. However, the studies were not designed to definitely establish the risk of use of metformin during lactation because of small sample size and limited adverse event data collected in infants.

8.3 Females and Males of Reproductive Potential

- Discuss the potential for unintended pregnancy with premenopausal women as therapy with RIOMET may result in ovulation in some anovulatory women.

8.4 Pediatric Use

1. The safety and effectiveness of RIOMET for the treatment of type 2 diabetes mellitus have been established in pediatric patients 10 to 16 years old. Safety and effectiveness of RIOMET have not been established in pediatric patients less than 10 years old.
2. Use of RIOMET in pediatric patients 10 to 16 years old for the treatment of type 2 diabetes mellitus is supported by evidence from adequate and well-controlled studies of metformin HCl tablets in adults with additional data from a controlled clinical study of metformin HCl tablets in pediatric patients 10 to 16 years old with type 2 diabetes mellitus, which demonstrated a similar response in glycemic control to that seen in adults [see Clinical Studies (14)]. In this study, adverse reactions were similar to those described in adults. A maximum daily dose of 2,000 mg of RIOMET is recommended. [See Dosage and Administration (2.2).]

8.5 Geriatric Use

1. Controlled clinical studies of metformin HCl tablets did not include sufficient numbers of elderly patients to determine whether they respond differently from younger patients. In general, dose selection for an elderly patient should be cautious, usually starting at the low end of the dosing range, reflecting the greater frequency of decreased hepatic, renal, or cardiac function, and of concomitant disease or other drug therapy and the higher risk of lactic acidosis. Assess renal function more frequently in elderly patients [see Warnings and Precautions (5.1)].

8.6 Renal Impairment

- Metformin is substantially excreted by the kidney, and the risk of metformin accumulation and lactic acidosis increases with the degree of renal impairment. RIOMET is contraindicated in severe renal impairment, patients with an estimated glomerular filtration rate (eGFR) below 30 mL/min/1.73 m^2 [see Dosage and Administration (2.3), Contraindications (4), Warnings and Precautions (5.1), and Clinical Pharmacology (12.3)].

8.7 Hepatic Impairment

- Use of metformin in patients with hepatic impairment has been associated with some cases of lactic acidosis. RIOMET is not recommended in patients with hepatic impairment. [see Warnings and Precautions (5.1)].

10 OVERDOSAGE

- Overdose of metformin hydrochloride has occurred, including ingestion of amounts greater than 50 grams. Hypoglycemia was reported in approximately 10% of cases, but no causal association with metformin has been established. Lactic acidosis has been reported in approximately 32% of metformin overdose cases [see Warnings and Precautions (5.1)]. Metformin is dialyzable with a clearance of up to 170 mL/min under good hemodynamic conditions. Therefore, hemodialysis may be useful for removal of accumulated drug from patients in whom metformin overdosage is suspected.

11 DESCRIPTION

RIOMET oral solution contains the biguanidine antihyperglycemic agent metformin in the form of monohydrochloride salt. Metformin hydrochloride, is N,N-dimethylimidodicarbonimidic diamide hydrochloride. The structural formula is shown as:

Metformin hydrochloride, USP is a white crystalline powder with a molecular formula of C 4H11N5•HCl and a molecular weight of 165.62. Metformin hydrochloride, USP 2.0 g is soluble in 20 mL of water. The pKa of metformin is 12.4. The pH of a 1% aqueous solution of metformin hydrochloride is 6.68. It is freely soluble in water; slightly soluble in alcohol; practically insoluble in acetone and in methylene chloride.

RIOMET (Cherry Flavor) contains 500 mg of metformin hydrochloride (the equivalent of 389.93 mg metformin) per 5 mL and the following inactive ingredients: Artificial cherry flavor, hydrochloric acid, potassium bicarbonate, purified water, saccharin calcium, and xylitol.

RIOMET (Strawberry Flavor) contains 500 mg of metformin hydrochloride (the equivalent of 389.93 mg metformin) per 5 mL and the following inactive ingredients: Hydrochloric acid, N&A strawberry flavor (propylene glycol and glycerin), potassium bicarbonate, purified water, sucralose, and xylitol.

12 CLINICAL PHARMACOLOGY

12.1 Mechanism of Action

- Metformin is an antihyperglycemic agent which improves glucose tolerance in patients with type 2 diabetes mellitus, lowering both basal and postprandial plasma glucose. Metformin decreases hepatic glucose production, decreases intestinal absorption of glucose, and improves insulin sensitivity by increasing peripheral glucose uptake and utilization. With metformin therapy, insulin secretion remains unchanged while fasting insulin levels and day-long plasma insulin response may decrease.

12.3 Pharmacokinetics

1. Two pharmacokinetic studies performed in healthy volunteers to evaluate the bioavailability of RIOMET in comparison with metformin HCl tablets under fasting and fed conditions showed that the rate and extent of absorption of RIOMET was found to be comparable to that of metformin HCl tablets under fasting or fed conditions (see Table 3).

Table 3: Select Mean (± S.D.) Pharmacokinetic Parameters Following Single Oral Doses of 1000 mg RIOMET and Metformin HCl tablets in healthy, nondiabetic adults (n = 36) under fed and fasting conditions
Formulation | Cmax (ng/mL) | AUC0-∞ (ng.h/mL) | Tmax (h)
Study 1- Fasting state
RIOMET | 1540.1 ± 451.1 | 9069.6 ± 2593.6 | 2.2 ± 0.5
Metformin HCl Tablets | 1885.1 ± 498.5 | 11100.1 ± 2733.1 | 2.5 ± 0.6
T/R Ratio X 100 (90% confidence interval) | 81.2; (76.3 to 86.4) | 81.2; (76.9 to 85.6) | -
Study 2- Fed State
RIOMET | 1235.3 ± 177.7 | 8950.1 ± 1381.2 | 4.1 ± 0.8
Metformin HCl Tablets | 1361 ± 298.8 | 9307.7 ± 1839.8 | 3.7 ± 0.8
T/R Ratio X 100 (90% confidence interval) | 91.8; (87.4 to 96.5) | 97.0; (92.9 to 101.2) | -

1. T-test product (RIOMET)
2. R-reference product (immediate release metformin HCl tablets)
3. Studies using single oral doses of metformin HCl tablets 500 mg to 1,500 mg, and 850 mg to 2,550 mg, indicate that there is a lack of dose proportionality with increasing doses, which is due to decreased absorption rather than an alteration in elimination. At usual clinical doses and dosing schedules of metformin, steady state plasma concentrations of metformin are reached within 24 to 48 hours and are generally < 1 mcg/mL.
4. Effect of food: The food-effect study assessed the effects of a high fat/high calorie meal and a low fat/low calorie meal on the bioavailability of RIOMET in comparison with administration in the fasted state, in healthy volunteers. The extent of absorption was increased by approximately 16% and 13% with the low fat/low calorie meal and the high fat/high calorie meal, respectively, compared with the administration in the fasted state. The rate and extent of absorption with high fat/high calorie and low fat/ low calorie meal were similar. The mean tmax was 2.5 hours under fasting conditions as compared to 3.9 hours with both low fat/ low calorie meal and high fat/high calorie meals (see Table 4).

Table 4: Select Mean (± S.D.) Metformin Pharmacokinetic Parameters Following Single Oral Doses of 1,000 mg RIOMET in healthy, nondiabetic adults (n = 33) under fed (high fat/high calorie meal and low fat/low calorie meal) and fasting conditions (study 3)
Meal type | Cmax; (ng/mL) | AUC0-∞; (ng.h/mL) | tmax; (h)
Fasting (F) | 1641.5 ± 551.8 | 9982.9 ± 2544.5 | 2.5 ± 0.9
Low fat/ low calorie meal (L) | 1525.8 ± 396.7 | 11542.0 ± 2947.5 | 3.9 ± 0.6
High fat/high calorie meal (H) | 1432.5 ± 346.8 | 11184.5 ± 2446.1 | 3.9 ± 0.8
L/F Ratio X 100 (90% confidence interval) | 94.6; (84.0 to 106.5) | 115.6; (103.6 to 128.9) | -
H/F Ratio X 100 (90% confidence interval) | 89.4; (79.4 to 100.6) | 112.6; (100.9 to 125.6) | -
L/H Ratio X 100 (90% confidence interval) | 105.8; (94.0 to 119.2) | 102.7; (92.0 to 114.6) | -

1. Distribution
2. The apparent volume of distribution (V/F) of metformin following single oral doses of metformin HCl 850 mg averaged 654 ± 358 L. Metformin is negligibly bound to plasma proteins. Metformin partitions into erythrocytes, most likely as a function of time.
3. Metabolism
4. Intravenous single-dose studies in normal subjects demonstrate that metformin is excreted unchanged in the urine and does not undergo hepatic metabolism (no metabolites have been identified in humans) nor biliary excretion.
5. Elimination
6. Renal clearance (see Table 5) is approximately 3.5 times greater than creatinine clearance, which indicates that tubular secretion is the major route of metformin elimination. Following oral administration, approximately 90% of the absorbed drug is eliminated via the renal route within the first 24 hours, with a plasma elimination half-life of approximately 6.2 hours. In blood, the elimination half-life is approximately 17.6 hours, suggesting that the erythrocyte mass may be a compartment of distribution.
7. Specific Populations
8. Renal Impairment
9. In patients with decreased renal function the plasma and blood half-life of metformin is prolonged and the renal clearance is decreased (see Table 5) [See Dosage and Administration (2.3), Contraindications (4), Warnings and Precautions (5.1) and Use in Specific Populations (8.6)].
10. Hepatic Impairment
11. No pharmacokinetic studies of metformin have been conducted in patients with hepatic impairment [See Warnings and Precautions (5.1) and Use in Specific Populations (8.7)].
12. Geriatrics
13. Limited data from controlled pharmacokinetic studies of metformin HCl tablets in healthy elderly subjects suggest that total plasma clearance of metformin is decreased, the half-life is prolonged, and Cmax is increased, compared to healthy young subjects. It appears that the change in metformin pharmacokinetics with aging is primarily accounted for by a change in renal function (see Table 5). [See Warnings and Precautions (5.1) and Use in Specific Populations (8.5)].
14. Table 5: Select Mean (±S.D.) Metformin Pharmacokinetic ParametersFollowing Single or Multiple Oral Doses of Metformin HCl Tablets

1. Subject Groups: 2. Metformin HCl dosea 3. (number of subjects) | 1. Cmaxb 2. (mcg/mL) | 1. Tmaxc 2. (hrs) | 1. Renal Clearance 2. (mL/min)
1. Healthy, nondiabetic adults:
1. 500 mg single dose (24) | 1. 1.03 (± 0.33) | 1. 2.75 (±0.81) | 1. 600 (±132)
1. 850 mg single dose (74)d | 1. 1.60 (±0.38) | 1. 2.64 (±0.82) | 1. 552 (±139)
1. 850 mg three times daily for 19 dosese (9) | 1. 2.01 (±0.42) | 1. 1.79 (±0.94) | 1. 642 (±173)
1. Adults with type 2 diabetes mellitus:
1. 850 mg single dose (23) | 1. 1.48 (±0.5) | 1. 3.32 (±1.08) | 1. 491 (±138)
1. 850 mg three times daily for 19 dosese (9) | 1. 1.90 (±0.62) | 1. 2.01 (±1.22) | 1. 550 (±160)
1. Elderlyf, healthy nondiabetic adults:
1. 850 mg single dose (12) | 1. 2.45 (±0.70) | 1. 2.71 (±1.05) | 1. 412 (±98)
1. Renal-impaired adults:
1. 850 mg single dose 2. Mild (CLcr g 61 to 90 mL/min) (5) | 1. 1.86 (±0.52) | 1. 3.20 (±0.45) | 1. 384 (±122)
1. Moderate (CLcr 31 to 60 mL/min) (4) | 1. 4.12 (±1.83) | 1. 3.75 (±0.50) | 1. 108 (±57)
1. Severe (CLcr 10 to 30 mL/min) (6) | 1. 3.93 (±0.92) | 1. 4.01 (±1.10) | 1. 130 (±90)

1. a All doses given fasting except the first 18 doses of the multiple dose studies
2. bPeak plasma concentration
3. cTime to peak plasma concentration
4. d Combined results (average means) of five studies: mean age 32 years (range 23 to 59 years)
5. e Kinetic study done following dose 19, given fasting
6. f Elderly subjects, mean age 71 years (range 65 to 81 years)
7. g CLcr = creatinine clearance normalized to body surface area of 1.73 m^2
8. Pediatrics
9. After administration of a single oral metformin HCl 500 mg tablet with food, geometric mean metformin Cmax and AUC differed less than 5% between pediatric type 2 diabetic patients (12 to 16 years of age) and gender- and weight-matched healthy adults (20 to 45 years of age), all with normal renal function.
10. Gender
11. Metformin pharmacokinetic parameters did not differ significantly between normal subjects and patients with type 2 diabetes mellitus when analyzed according to gender (males = 19, females = 16).
12. Race
13. No studies of metformin pharmacokinetic parameters according to race have been performed.
14. Drug Interactions
15. In VivoAssessment of Drug Interactions
16. Table 6: Effect of Coadministered Drug on Plasma Metformin SystemicExposure

1. Coadministered 2. Drug | 1. Dose of Coadministered 2. Drug* | 1. Dose of 2. Metformin HCl* | 1. Geometric Mean Ratio 2. (ratio with/without coadministered drug) No Effect = 1.00
1. Coadministered 2. Drug | 1. Dose of Coadministered 2. Drug* | 1. Dose of 2. Metformin HCl* |  | 1. AUC† | 1. Cmax
1. No dosing adjustments required for the following:
1. Glyburide | 1. 5 mg | 1. 850 mg | 1. metformin | 1. 0.91‡ | 1. 0.93‡
1. Furosemide | 1. 40 mg | 1. 850 mg | 1. metformin | 1. 1.09‡ | 1. 1.22‡
1. Nifedipine | 1. 10 mg | 1. 850 mg | 1. metformin | 1. 1.16 | 1. 1.21
1. Propranolol | 1. 40 mg | 1. 850 mg | 1. metformin | 1. 0.90 | 1. 0.94
1. Ibuprofen | 1. 400 mg | 1. 850 mg | 1. metformin | 1. 1.05‡ | 1. 1.07‡
1. Cationic drugs eliminated by renal tubular secretion may reduce metformin elimination [See Warnings and Precautions (5.1) and Drug Interactions (7).]
1. Cimetidine | 1. 400 mg | 1. 850 mg | 1. metformin | 1. 1.40 | 1. 1.61
1. Carbonic anhydrase inhibitors may cause metabolic acidosis [See Warnings and Precautions (5.1) and Drug Interactions (7).]
1. Topiramate | 1. 100 mg§ | 1. 500 mg§ | 1. metformin | 1. 1.25§ | 1. 1.17

1. * All metformin HCl and coadministered drugs were given as single doses
2. † AUC = AUC (INF)
3. ‡ Ratio of arithmetic means
4. § At steady state with topiramate 100 mg every 12 hours and metformin 500 mg every 12 hours; AUC = AUC0-12h
5. Table 7: Effect of Metformin on Coadministered Drug Systemic Exposure

1. Coadministered 2. Drug | 1. Dose of 2. Coadministered Drug* | 1. Dose of 2. Metformin HCl* | 1. Geometric Mean Ratio (ratio with/without metformin) No Effect = 1.00
1. Coadministered 2. Drug | 1. Dose of 2. Coadministered Drug* | 1. Dose of 2. Metformin HCl* |  | 1. AUC† | 1. Cmax
1. No dosing adjustments required for the following:
1. Glyburide | 1. 5 mg | 1. 850 mg | 1. glyburide | 1. 0.78‡ | 1. 0.63‡
1. Furosemide | 1. 40 mg | 1. 850 mg | 1. furosemide | 1. 0.87‡ | 1. 0.69‡
1. Nifedipine | 1. 10 mg | 1. 850 mg | 1. nifedipine | 1. 1.10§ | 1. 1.08
1. Propranolol | 1. 40 mg | 1. 850 mg | 1. propranolol | 1. 1.01§ | 1. 1.02
1. Ibuprofen | 1. 400 mg | 1. 850 mg | 1. ibuprofen | 1. 0.97¶ | 1. 1.01¶
1. Cimetidine | 1. 400 mg | 1. 850 mg | 1. cimetidine | 1. 0.95§ | 1. 1.01

1. * All metformin HCl and coadministered drugs were given as single doses
2. † AUC = AUCinf unless otherwise noted
3. ‡ Ratio of arithmetic means, p-value of difference < 0.05
4. § AUC0-24 hr reported
5. ¶ Ratio of arithmetic means

13 NONCLINICAL TOXICOLOGY

13.1 Carcinogenesis, Mutagenesis, Impairment of Fertility

1. Long-term carcinogenicity studies have been performed in rats (dosing duration of 104 weeks) and mice (dosing duration of 91 weeks) at doses up to and including 900 mg/kg/day and 1,500 mg/kg/day, respectively. These doses are both approximately 3 times the maximum recommended human daily dose of 2,550 mg based on body surface area comparisons. No evidence of carcinogenicity with metformin was found in either male or female mice. Similarly, there was no tumorigenic potential observed with metformin in male rats. There was, however, an increased incidence of benign stromal uterine polyps in female rats treated with 900 mg/kg/day.
2. There was no evidence of a mutagenic potential of metformin in the following in vitro tests: Ames test (S. typhimurium), gene mutation test (mouse lymphoma cells), or chromosomal aberrations test (human lymphocytes). Results in the in vivo mouse micronucleus test were also negative.
3. Fertility of male or female rats was unaffected by metformin when administered at doses as high as 600 mg/kg/day, which is approximately 2 times the maximum recommended human daily dose of 2,550 mg based on body surface area comparisons.

14 CLINICAL STUDIES

1. Adult Clinical Studies
2. A double-blind, placebo-controlled, multicenter US clinical trial involving obese patients with type
3. 2 diabetes mellitus whose hyperglycemia was not adequately controlled with dietary management alone (baseline fasting plasma glucose [FPG] of approximately 240 mg/dL) was conducted. Patients were treated with metformin HCl tablets (up to 2,550 mg/day) or placebo for 29 weeks. The results are presented in Table 8.
4. Table 8: Mean Change in Fasting Plasma Glucose and HbA1c at Week 29Comparing Metformin HCl Tablets vs Placebo in Patients with Type 2Diabetes Mellitus

 | 1. Metformin HCL 2. Tablets (n=141) | 1. Placebo 2. (n=145) | 1. p-Value
1. FPG (mg/dL) 2. Baseline 3. Change at FINAL VISIT | 1. 241.5 2. –53.0 | 1. 237.7 2. 6.3 | 1. NS* 2. 0.001
1. Hemoglobin A1c (%) 2. Baseline 3. Change at FINAL VISIT | 1. 8.4 2. –1.4 | 1. 8.2 2. 0.4 | 1. NS* 2. 0.001

1. * Not statistically significant
2. Mean baseline body weight was 201 lbs and 206 lbs in the metformin HCl tablet and placebo arms, respectively. Mean change in body weight from baseline to week 29 was -1.4 lbs and -2.4 lbs in the metformin HCl tablet and placebo arms, respectively.
3. A 29-week, double-blind, placebo-controlled study of metformin HCl tablet and glyburide, alone and in combination, was conducted in obese patients with type 2 diabetes mellitus who had failed to achieve adequate glycemic control while on maximum doses of glyburide (baseline FPG of approximately 250 mg/dL). Patients randomized to the combination arm started therapy with metformin HCl tablet 500 mg and glyburide 20 mg. At the end of each week of the first 4 weeks of the trial, these patients had their dosages of metformin HCl increased by 500 mg if they had failed to reach target fasting plasma glucose. After week 4, such dosage adjustments were made monthly, although no patient was allowed to exceed metformin HCl 2,500 mg. Patients in the metformin only arm (metformin HCl plus placebo) discontinued glyburide and followed the same titration schedule. Patients in the glyburide arm continued the same dose of glyburide. At the end of the trial, approximately 70% of the patients in the combination group were taking metformin HCl 2,000 mg/glyburide 20 mg or metformin HCl 2,500 mg/glyburide 20 mg. The results are displayed in Table 9.
4. Table 9: Mean Change in Fasting Plasma Glucose and HbA1c at Week 29Comparing Metformin HCl Tablets/Glyburide (Comb) vs Glyburide (Glyb) vs Metformin HCl Tablets (GLU): in Patients with Type 2 Diabetes Mellitus with Inadequate Glycemic Control on Glyburide

 | Comb; (n = 213) | Glyb; (n = 209) | GLU; (n = 210) | p-Values
 | Comb; (n = 213) | Glyb; (n = 209) | GLU; (n = 210) | Glyb vs Comb | GLU vs Comb | GLU vs Glyb
1. Fasting Plasma Glucose (mg/dL) 2. Baseline 3. Change at FINAL VISIT | 1. 250.5 2. –63.5 | 1. 247.5 2. 13.7 | 1. 253.9 2. –0.9 | NS*; 0.001 | NS*; 0.001 | NS*; 0.025
1. Hemoglobin A1c (%) 2. Baseline 3. Change at FINAL VISIT | 1. 8.8 2. –1.7 | 1. 8.5 2. 0.2 | 1. 8.9 2. –0.4 | NS*; 0.001 | NS*; 0.001 | 0.007; 0.001

1. * Not statistically significant
2. Mean baseline body weight was 202 lbs, 203 lbs, and 204 lbs in the metformin HCl tablet/glyburide, glyburide, and metformin HCl tablet arms, respectively. Mean change in body weight from baseline to week 29 was 0.9 lbs, -0.7 lbs, and -8.4 lbs in the metformin HCl tablet/glyburide, glyburide, and metformin HCl tablet arms, respectively.
3. Pediatric Clinical Studies
4. A double-blind, placebo-controlled study was conducted in pediatric patients aged 10 to 16 years with type 2 diabetes mellitus (mean FPG 182.2 mg/dL), where patients were treated with metformin HCl tablets (up to 2,000 mg/day) for up to 16 weeks (mean duration of treatment 11 weeks). The results are displayed in Table 10.
5. Table 10: Mean Change in Fasting Plasma Glucose at Week 16 Comparing Metformin HCl Tablets vs Placebo in Pediatric Patientsa with Type 2Diabetes Mellitus

 | 1. Metformin HCl Tablets | 1. Placebo | 1. p-Value
1. FPG (mg/dL) 2. Baseline 3. Change at FINAL VISIT | 1. (n = 37) 2. 162.4 3. –42.9 | 1. (n = 36); 192.3; 21.4 | 1. <0.001

1. aPediatric patients mean age 13.8 years (range 10 to16 years)
2. Mean baseline body weight was 205 lbs and 189 lbs in the metformin HCl tablet and placebo arms, respectively. Mean change in body weight from baseline to week 16 was -3.3 lbs and -2.0 lbs in the metformin HCl tablet and placebo arms, respectively.

16 HOW SUPPLIED/STORAGE AND HANDLING

How Supplied

1. RIOMET 500 mg per 5 mL (100 mg/mL) oral solution is supplied in bottles with child-resistant caps and a dosing cup as follows:

Flavor | Appearance | Size | NDC
Cherry | clear, colorless solution | 4 ounce (118 mL) | 10631-206-01
Cherry | clear, colorless solution | 16 ounce (473 mL) | 10631-206-02
Strawberry | clear, colorless to light yellow solution | 4 ounce (118 mL) | 10631-238-01
Strawberry | clear, colorless to light yellow solution | 16 ounce (473 mL) | 10631-238-02

Storage

1. Store at 15° - 30° C (59° - 86° F) [See USP Controlled Room Temperature].

17 PATIENT COUNSELING INFORMATION

1. Advise the patient to read the FDA-approved patient labeling (Patient Information).
2. Administration:
3. Instruct patients or caregivers to use the supplied dosing cup to measure the prescribed amount of medication. Inform patients that additional RIOMET dosing cups or oral dosing syringes may be obtained from their pharmacy.
4. Lactic Acidosis:
5. Explain the risks of lactic acidosis, its symptoms, and conditions that predispose to its development. Advise patients to discontinue RIOMET immediately and to promptly notify their healthcare provider if unexplained hyperventilation, myalgias, malaise, unusual somnolence or other nonspecific symptoms occur. Counsel patients against excessive alcohol intake and inform patients about importance of regular testing of renal function while receiving RIOMET. Instruct patients to inform their doctor that they are taking RIOMET prior to any surgical or radiological procedure, as temporary discontinuation may be required [see Warnings and Precautions (5.1)].
6. Hypoglycemia
7. Inform patients that hypoglycemia may occur when RIOMET is coadministered with oral sulfonylureas and insulin. Explain to patients receiving concomitant therapy the risks of hypoglycemia, its symptoms and treatment, and conditions that predispose to its development [see Warnings and Precautions (5.3)].
8. Vitamin B12 Deficiency:
9. Inform patients about importance of regular hematological parameters while receiving RIOMET [see Warnings and Precautions (5.2)].
10. Females of Reproductive Age:
11. Inform females that treatment with RIOMET may result in ovulation in some premenopausal anovulatory women which may lead to unintended pregnancy [see Use in Specific Populations (8.3)].
12. RIOMET is a registered trademark of Sun Pharmaceutical Industries Limited.
13. Manufactured by:
14. Mikart, LLC
15. Atlanta, GA 30318
16. Distributed by:
17. Sun Pharmaceutical Industries, Inc.
18. Cranbury, NJ 08512
19. November 2018 FDA-11

Patient Medication Information

- PATIENT INFORMATION
- RIOMET (ree oh met)
- (metformin hydrochloride)
- oral solution
- What is the most important information I should know about RIOMET?
- RIOMET can cause serious side effects, including:
- Lactic Acidosis. Metformin hydrochloride, the medicine in RIOMET, can cause a rare, but serious side effect called lactic acidosis (a build-up of lactic acid in the blood) that can cause death. Lactic acidosis is a medical emergency and must be treated in a hospital.
- Stop taking RIOMET and call your healthcare provider right away if you get any of the following symptoms of lactic acidosis:

- feel very weak and tired

- have unusual sleepiness or sleep longer than usual

- have unusual (not normal) muscle pain

- feel cold, especially in your arms and legs

- have trouble breathing

- feel dizzy or lightheaded

- have unexplained stomach or intestinal problems with nausea and vomiting, or diarrhea

- have a slow or irregular heartbeat

1. You have a higher chance of getting lactic acidosis if you:
2. have moderate to severe kidney problems. See “Do not take RIOMET if you”
3. have liver problems.
4. have congestive heart failure that requires treatment with medicines.
5. drink a lot of alcohol (very often or short-term “binge” drinking).
6. get dehydrated (lose a large amount of body fluids). This can happen if you are sick with a fever, vomiting, or diarrhea. Dehydration can also happen when you sweat a lot with activity or exercise and do not drink enough fluids.
7. have certain x-ray tests with injectable dyes or contrast agents.
8. have surgery.
9. have a heart attack, severe infection, or stroke.
10. are 65 years of age or older.
11. Tell your healthcare provider if you have any of the problems in the list above.
12. Tell your healthcare provider that you are taking RIOMET before you have surgery or x-ray tests. Your healthcare provider may need to stop RIOMET for a while if you have surgery or certain x-ray tests.
13. RIOMET can have other serious side effects. See “What are the possible side effects of RIOMET?”
14. What is RIOMET?
15. RIOMET is a prescription medicine that contains metformin hydrochloride. RIOMET is used with diet and exercise to help control high blood sugar (hyperglycemia) in adults and children 10 years of age and older with type 2 diabetes.
16. It is not known if RIOMET is safe and effective in children under 10 years of age.
17. Do not take RIOMET if you:
18. have severe kidney problems.
19. are allergic to the metformin hydrochloride or any of the ingredients in RIOMET. See the end of this Patient Information leaflet for a complete list of ingredients in RIOMET.
20. have a condition called metabolic acidosis including diabetic ketoacidosis (high levels of certain acids called “ketones” in your blood or urine).
21. Before taking RIOMET tell your healthcare provider about all your medical conditions, including if you:
22. have a history or risk for diabetic ketoacidosis. See “Do not take RIOMET if you?”
23. have kidney problems.
24. have liver problems.
25. have heart problems, including congestive heart failure.
26. are 65 years or older.
27. drink alcohol very often or drink a lot of alcohol in short-term “binge” drinking.
28. are taking insulin or a sulfonylurea medicine.
29. are pregnant or plan to become pregnant. It is not known if RIOMET will harm your unborn baby. If you are pregnant, talk with your healthcare provider about the best way to control your blood sugar while you are pregnant.
30. are a premenopausal woman who does not have periods regularly or at all. RIOMET can cause the release of an egg from an ovary in a woman (ovulation). This can increase your chance of getting pregnant.
31. are breastfeeding or plan to breastfeed. RIOMET can pass into your breast milk. Talk with your healthcare provider about the best way to feed your baby while you take RIOMET.
32. Tell your healthcare provider about all the medicines you take, including prescription and over-the-counter medicines, vitamins, and herbal supplements. Know the medicines you take. Keep a list of them to show your healthcare provider and pharmacist when you get a new medicine.
33. RIOMET may affect the way other medicines work, and other medicines may affect how RIOMET works.
34. How should I take RIOMET?
35. Take RIOMET exactly as your healthcare provider tells you.
36. Use the Riomet dosing cup to measure your dose. Ask your pharmacist for a dosing cup if you do not have one.
37. RIOMET should be taken with meals to help decrease an upset stomach.
38. When your body is under some types of stress, such as fever, trauma (such as a car accident), infection, or surgery, the amount of diabetes medicine that you need may change. Tell your healthcare provider right away if you have any of these problems.
39. Your healthcare provider should do blood tests to check how well your kidneys are working before and during your treatment with RIOMET.
40. Your healthcare provider will check your diabetes with regular blood tests, including your blood sugar levels and your hemoglobin A1C.
41. Low blood sugar (hypoglycemia) can happen more often when RIOMET is taken with certain other diabetes medicines. Talk to your healthcare provider about how to prevent, recognize and manage low blood sugar. See “What are the possible side effects of RIOMET?”
42. Check your blood sugar as your healthcare provider tells you to.
43. Stay on your prescribed diet and exercise program while taking RIOMET.
44. If you take too much RIOMET, call your healthcare provider, or go to the nearest hospital emergency room right away.
45. What should I avoid while taking RIOMET?
46. Do not drink a lot of alcoholic drinks while taking RIOMET. This means you should not binge drink for short periods, and you should not drink a lot of alcohol on a regular basis. Alcohol can increase the chance of getting lactic acidosis.
47. What are the possible side effects of RIOMET?
48. RIOMET may cause serious side effects, including:
49. See “What is the most important information I should know about RIOMET?”
50. Low vitamin B12 (vitamin B12 deficiency). Using RIOMET may cause a decrease in the amount of vitamin B12 in your blood, especially if you have had low vitamin B12 levels before. Your healthcare provider may do blood tests to check your vitamin B12 levels.
51. Low blood sugar (hypoglycemia). If you take RIOMET with another medicine that can cause lower blood sugar, such as a sulfonylurea or insulin, your risk of getting low blood sugar is higher. The dose of your sulfonylurea medicine or insulin may need to be lowered while you take RIOMET. Signs and symptoms of low blood sugar may include:

- headache

- hunger

- dizziness

- drowsiness

- fast heartbeat

- sweating

- weakness

- confusion

- irritability

- shaking or feeling jittery

1. Common side effects of RIOMET include:

- diarrhea

- indigestion

- nausea and vomiting

- stomach-area (abdominal) discomfort

- gassiness (flatulence)

- headache

- weakness or lack of energy (asthenia)

1. These are not all the possible side effects of RIOMET.
2. Call your doctor for medical advice about side effects. You may report side effects to FDA at 1-800-FDA-1088.
3. How should I store RIOMET?
4. Store at room temperature between 59°F to 86°F (15°C to 30°C). See insert.
5. Keep RIOMET and all medicines out of the reach of children.
6. General information about the safe and effective use of RIOMET.
7. Medicines are sometimes prescribed for purposes other than those listed in a Patient Information leaflet. Do not use RIOMET for a condition for which it was not prescribed. Do not give RIOMET to other people, even if they have the same symptoms that you have. It may harm them.
8. You can ask your pharmacist or healthcare provider for information about RIOMET that is written for health professionals.
9. What are the ingredients of RIOMET?
10. Active ingredients: metformin hydrochloride.
11. Inactive ingredients (Cherry Flavor): Artificial cherry flavor, hydrochloric acid, potassium bicarbonate, purified water, saccharin calcium, and xylitol.
12. Inactive ingredients (Strawberry Flavor): Hydrochloric acid, N&A strawberry flavor (propylene glycol and glycerin), potassium bicarbonate, purified water, sucralose, and xylitol.
  Manufactured by:
  Mikart, LLC
  Atlanta, GA 30318
  Distributed by:
  Sun Pharmaceutical Industries, Inc.
  Cranbury, NJ 08512

PACKAGE LABEL. PRINCIPAL DISPLAY PANEL

NDC 10631-238-02

Riomet®

(metformin hydrochloride oral solution)

500 mg/5 mL

Each 5 mL contains: 500 mg of metformin hydrochloride, USP.

Strawberry Flavor

Rx only

16 fl. oz.473 mL

Strawberry Flavor

Package/Label Display Panel

NDC 10631-206-02

Riomet®

(metformin hydrochloride oral solution)

500 mg/5 mL

Each 5 mL contains: 500 mg of metformin hydrochloride, USP.

Cherry Flavor

Rx only

16 fl. oz.473 mL

Cherry Flavor